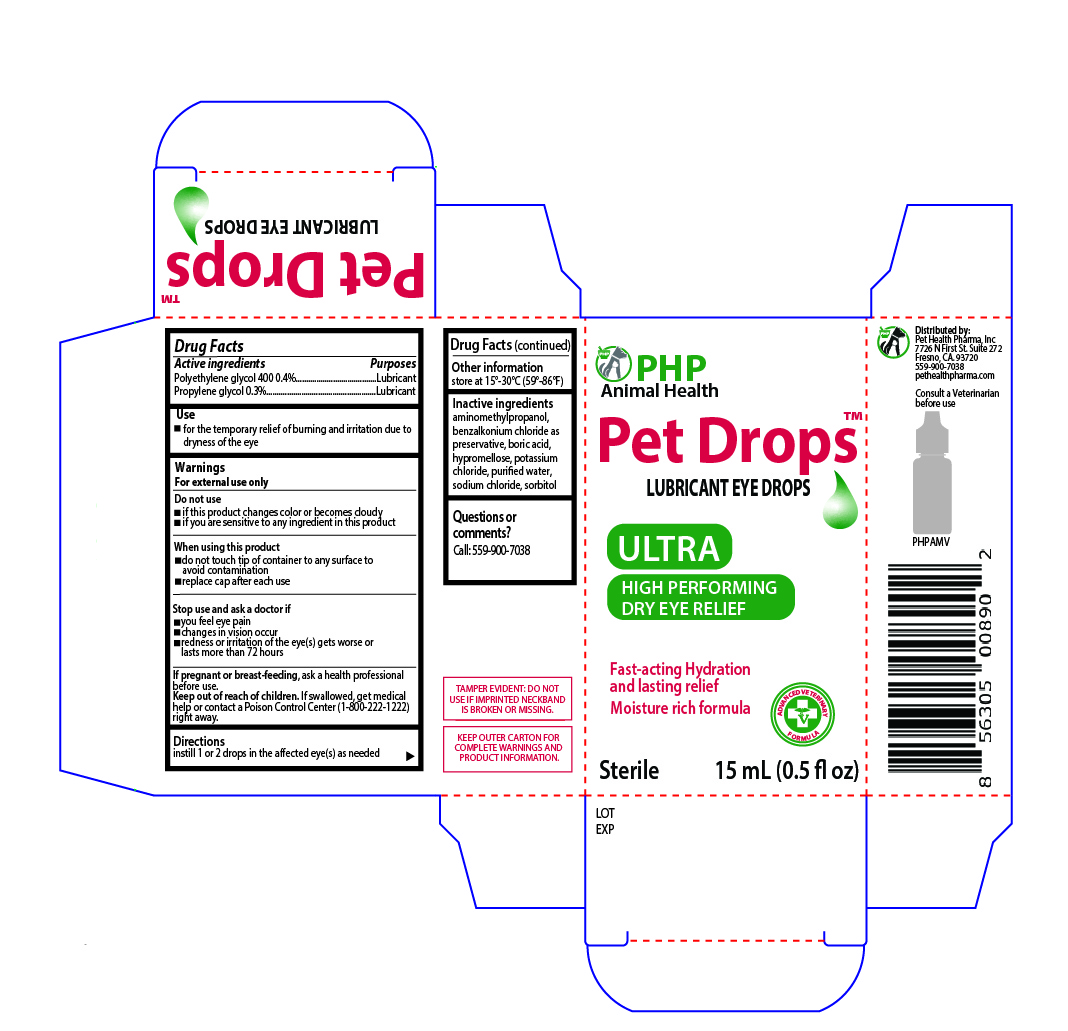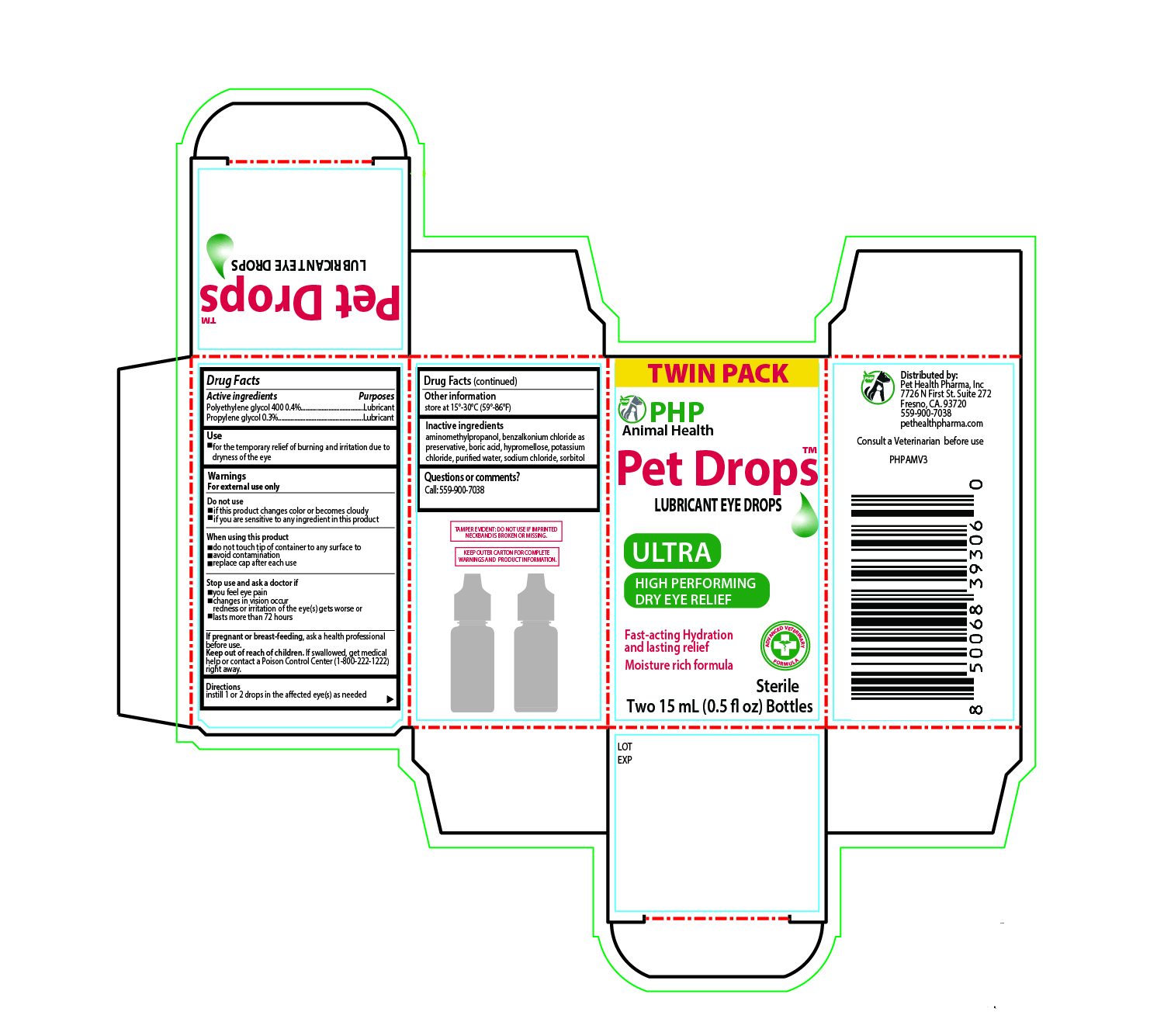 DRUG LABEL: Pet Drops Lubricant Eye Drops High Performance
NDC: 86176-301 | Form: SOLUTION/ DROPS
Manufacturer: Pet Health Pharma, LLC
Category: animal | Type: OTC ANIMAL DRUG LABEL
Date: 20251211

ACTIVE INGREDIENTS: POLYETHYLENE GLYCOL 400 0.4 g/100 mL; PROPYLENE GLYCOL 0.3 g/100 mL

Pet Drops Lubricant Eye Drops High Performance for Cats and Dogs

Active ingredients:

Polyethylene glycol 400 0.4%

Propylene glycol 0.3%

Purposes:

Lubricant

Lubricant

Use:

for the temporary relief of burning and irritation due to dryness of the eye

Warnings:

For external use only

Do not use

- if this product changes color or becomes cloudy
- if you are sensitive to any ingredient in this product

When using this product

- do not touch tip of container to any surface to avoid contamination
- replace cap after each use

Stop use and ask a doctor if

- you feel eye pain
- changes in vision occur
- redness or irritation of the eye(s) gets worse or lasts more than 72 hours

If pregnant or breast-feeding,
ask a health professional before use.

Keep out of reach of children.
If swallowed, get medical help or contact a Poison Control Center (1-800-222-1222) right away.

Direction:

shake well before using put 1 or 2 drops in the affected eyes as needed

Other information:

store at 15º-30ºC (59º-86ºF)

Inactive ingredients:

aminomethylpropanol, benzalkonium chloride as preservative, boric acid, hypromellose, potassium chloride, purified water, sodium chloride, sorbitol;

PRINCIPAL DISPLAY PANEL:

PHP Animal Health

Pet Drops

Lubricant Eye Drops

Ultra

HIGH PERFORMING
DRY EYE RELIEF

Fast-acting Hydration
and lasting relief

Moisture rich formula

Sterile 15 mL (0.5 fl oz)

SIDE PANEL:

Distributed by:
Pet Health Pharma, Inc
7726 N First St. Suite 272
Fresno, CA. 93720
559-900-7038
pethealthpharma.com

Consult a Veterinarian before use

ACTUAL SIZE

TAMPER EVIDENT: DO NOT USE IF IMPRINTED NECKBAND IS BROKEN OR MISSING

KEEP OUTER CARTON FOR COMPLETE WARNINGS AND PRODUCT INFORMATION.